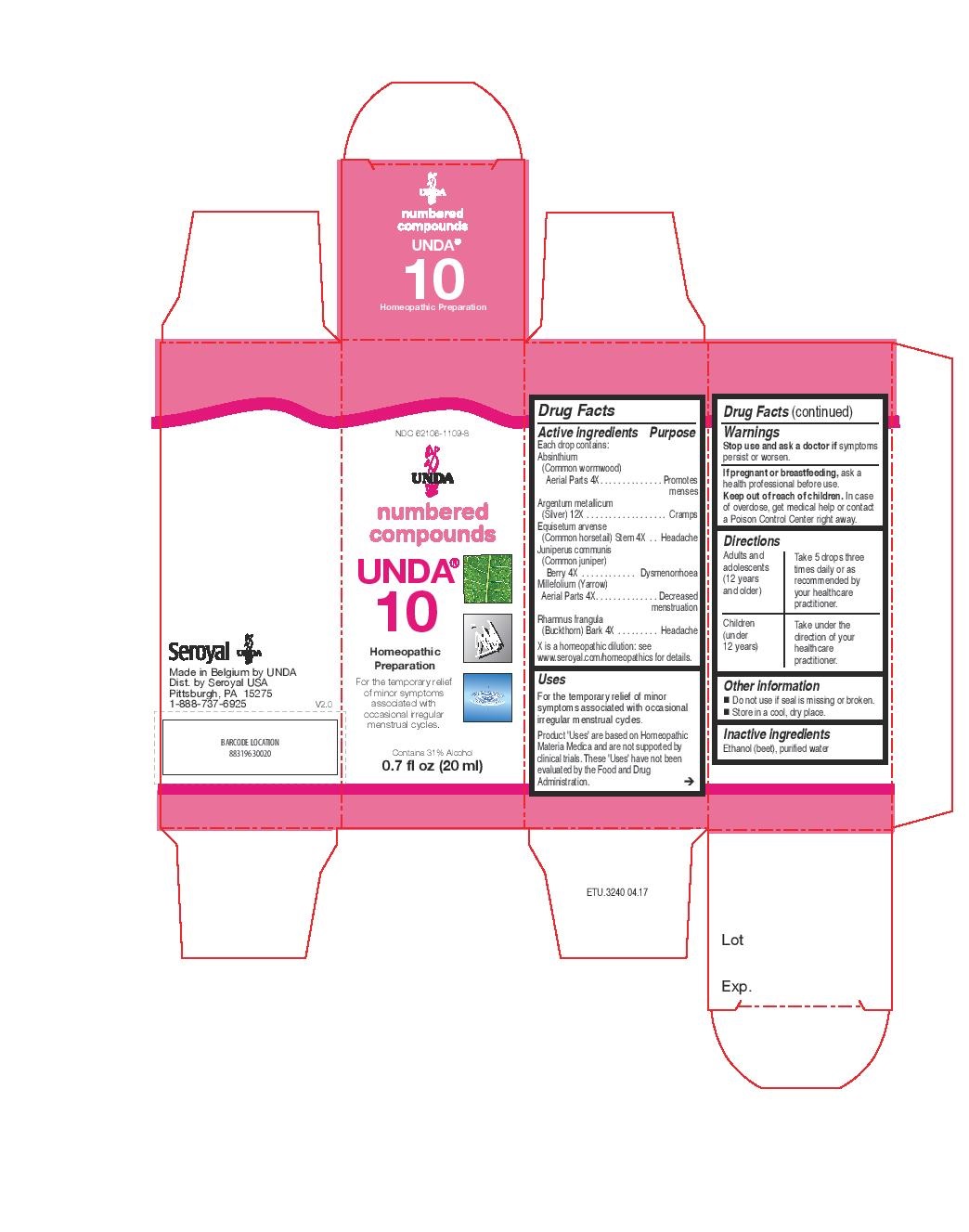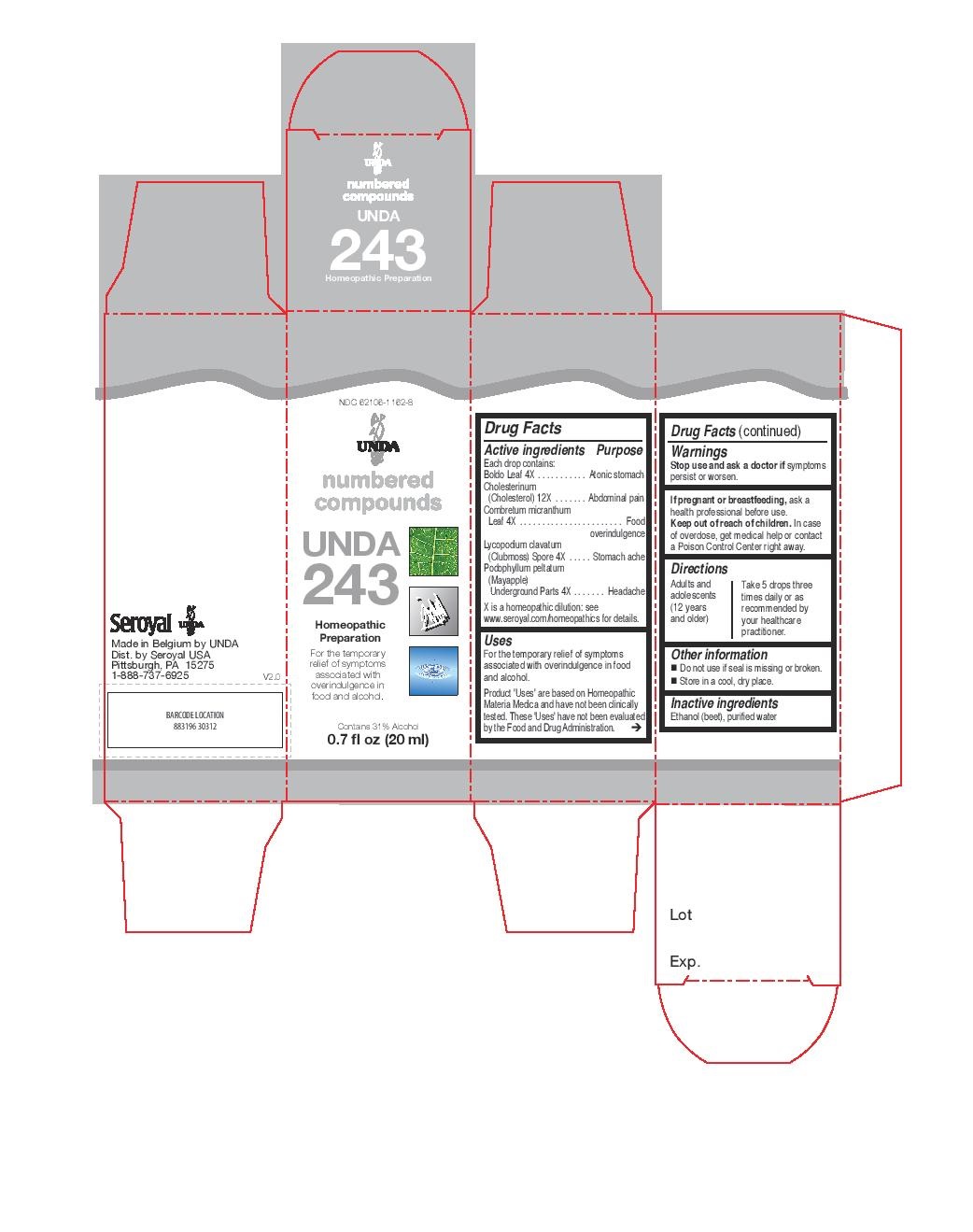 DRUG LABEL: UNDA 10
NDC: 62106-1109 | Form: LIQUID
Manufacturer: Seroyal USA
Category: homeopathic | Type: HUMAN OTC DRUG LABEL
Date: 20221108

ACTIVE INGREDIENTS: SILVER 12 [hp_X]/20 mL; EQUISETUM ARVENSE BRANCH 4 [hp_X]/20 mL; JUNIPER BERRY 4 [hp_X]/20 mL; WORMWOOD 4 [hp_X]/20 mL; ACHILLEA MILLEFOLIUM 4 [hp_X]/20 mL; FRANGULA ALNUS BARK 4 [hp_X]/20 mL
INACTIVE INGREDIENTS: ALCOHOL; WATER

Unda 10 and 243

Active ingredients

Each drop contains:
Absinthium (Common wormwood) Aerial Parts 4X
Argentum metallicum (Silver) 12X
Equisetum arvense (Common horsetail) Stem 4X
Juniperus communis (Common juniper) Berry 4X
Millefolium (Yarrow) Aerial Parts 4X
Rhamnus frangula (Buckthorn) Bark 4X

Uses

For the temporary relief of minor symptoms associated with occasional irregular menstrual cycles.

Warnings
Stop use and ask a doctor if symptoms persist or worsen.
If pregnant or breastfeeding, ask a health professional before use.
Keep out of reach of children.
In case of overdose, get medical help or contact a Poison Control Center right away.

Stop use and ask a doctor if symptoms persist or worsen.

PREGNANCY OR BREAST FEEDING

If pregnant or breastfeeding, ask a health professional before use.

Keep out of reach of children.

OVERDOSAGE

In case of overdose, get medical help or contact a Poison Control Center right away.

Inactive ingredients
Ethanol (beet), purified water

Other information
Do not use if seal is missing or broken.
Store in a cool, dry place.

Directions
Adults and adolescents (12 years and older): Take 5 drops three times daily or as
recommended by your healthcare practitioner.
Children (under 12 years): Take under the direction of your
healthcare practitioner.

Uses

For the temporary relief of minor symptoms associated with occasional irregular menstrual cycles.

Directions
Adults and adolescents (12 years and older): Take 5 drops three times daily or as
recommended by your healthcare practitioner.
Children (under 12 years): Take under the direction of your
healthcare practitioner.

Active ingredients

Each drop contains:
Boldo Leaf 4X
Cholesterinum (Cholesterol) 12X
Combretum micranthum Leaf 4X
Lycopodium clavatum (Clubmoss) Spore 4X
Podophyllum peltatum (Mayapple) Underground Parts 4X

Uses

For the temporary relief of symptoms associated with overindulgence in food and alcohol.

Warnings
Stop use and ask a doctor if symptoms persist or worsen.
If pregnant or breastfeeding, ask a health professional before use.
Keep out of reach of children.
In case of overdose, get medical help or contact a Poison Control Center right away.

Stop use and ask a doctor if symptoms persist or worsen.

PREGNANCY OR BREAST FEEDING

If pregnant or breastfeeding, ask a health professional before use.

Keep out of reach of children.

OVERDOSAGE

In case of overdose, get medical help or contact a Poison Control Center right away.

Inactive ingredients
Ethanol (beet), purified water

Other information
Do not use if seal is missing or broken.
Store in a cool, dry place.

Directions

Adults and adolescents (12 years and older): Take 5 drops three times daily or as
recommended by your healthcare practitioner.

Uses

For the temporary relief of symptoms associated with overindulgence in food and alcohol.

Directions
Adults and adolescents (12 years and older): Take 5 drops three
times daily or as recommended by your healthcare practitioner.

PACKAGE LABEL

NDC 62106-1109-8

UNDA
numbered compounds
UNDA 10
Homeopathic Preparation

For the temporary relief of minor symptoms
associated with occasional irregular menstrual cycles.
Contains 31% Alcohol
0.7 fl oz (20 mL)

PACKAGE LABEL

NDC 62106-1162-8

UNDA
numbered compounds
UNDA 243
Homeopathic Preparation

For the temporary relief of symptoms
associated with overindulgence in
food and alcohol.
Contains 31% Alcohol
0.7 fl oz (20 mL)